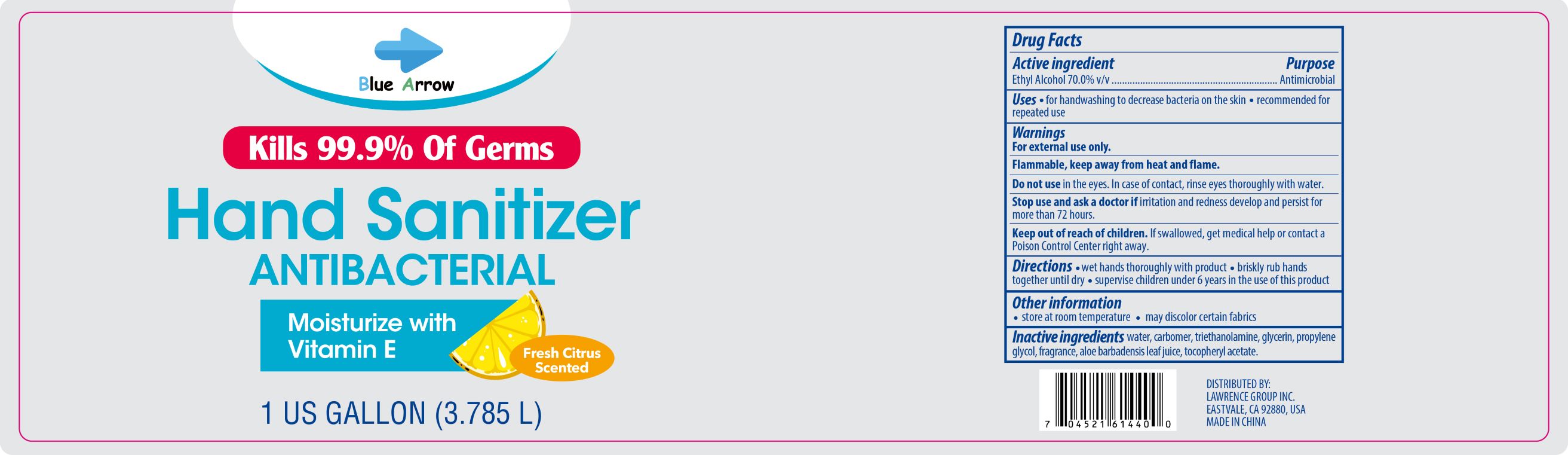 DRUG LABEL: Blue Arrow Hand Sanitizer 1 Gallon
NDC: 58503-147 | Form: LIQUID
Manufacturer: China Ningbo Shangge Technology Co., Ltd.
Category: otc | Type: HUMAN OTC DRUG LABEL
Date: 20200908

ACTIVE INGREDIENTS: ALCOHOL 70 mL/100 mL
INACTIVE INGREDIENTS: ALPHA-TOCOPHEROL ACETATE; ALOE VERA LEAF; PROPYLENE GLYCOL; GLYCERIN; WATER; CARBOMER HOMOPOLYMER, UNSPECIFIED TYPE

Active Ingredient(s)

Ethyl Alcohol 70% v/v.

Purpose

Antimicrobial

Use

- for handwashing to decrease bacteria on the skin
- recommended for repeated use

Warnings

For external use only. Flammable, keep away from heat and flame

Do not use in the eyes. In case of contact, rinse eyes thoroughly with water.

Stop use and ask a doctor if irritation and redness develop and persist for more than 72 hours.

Keep out of reach of children. If swallowed, get medical help or contact a Poison Control Center right away.

Directions

- wet hands thoroughly with product
- briskly rub hands together until dry
- supervise children under 6 years in the use of this product

Other information

- store at room temperature
- may discolor certain fabrics

Inactive ingredients

water, carbomer, triethanolamine, glycerin, propylene glycol, fragrance, aloe barbadensis leaf juice, tocopheryl acetate.